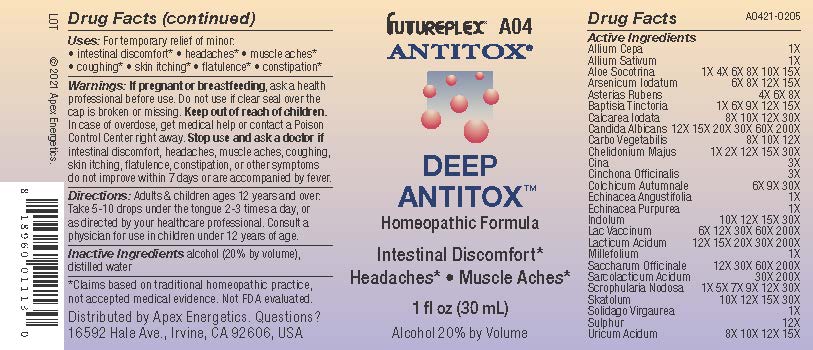 DRUG LABEL: A04
NDC: 63479-0104 | Form: SOLUTION/ DROPS
Manufacturer: Apex Energetics Inc.
Category: homeopathic | Type: HUMAN OTC DRUG LABEL
Date: 20240108

ACTIVE INGREDIENTS: ONION 1 [hp_X]/1 mL; ECHINACEA ANGUSTIFOLIA WHOLE 1 [hp_X]/1 mL; SUCROSE 200 [hp_X]/1 mL; SCROPHULARIA NODOSA 30 [hp_X]/1 mL; CANDIDA ALBICANS 200 [hp_X]/1 mL; CALCIUM IODIDE 30 [hp_X]/1 mL; ACTIVATED CHARCOAL 12 [hp_X]/1 mL; CHELIDONIUM MAJUS 30 [hp_X]/1 mL; ARTEMISIA CINA PRE-FLOWERING TOP 3 [hp_X]/1 mL; COLCHICUM AUTUMNALE BULB 30 [hp_X]/1 mL; ECHINACEA PURPUREA 1 [hp_X]/1 mL; ACHILLEA MILLEFOLIUM 1 [hp_X]/1 mL; COW MILK 200 [hp_X]/1 mL; SULFUR 12 [hp_X]/1 mL; URIC ACID 15 [hp_X]/1 mL; CINCHONA OFFICINALIS BARK 3 [hp_X]/1 mL; BAPTISIA TINCTORIA ROOT 15 [hp_X]/1 mL; SOLIDAGO VIRGAUREA FLOWERING TOP 1 [hp_X]/1 mL; GARLIC 1 [hp_X]/1 mL; ALOE 15 [hp_X]/1 mL; ARSENIC TRIIODIDE 15 [hp_X]/1 mL; ASTERIAS RUBENS 8 [hp_X]/1 mL; INDOLE 30 [hp_X]/1 mL; LACTIC ACID, DL- 200 [hp_X]/1 mL; LACTIC ACID, L- 200 [hp_X]/1 mL; SKATOLE 30 [hp_X]/1 mL
INACTIVE INGREDIENTS: ALCOHOL; WATER

A04

Active Ingredients
Allium Cepa | 1X
Allium Sativum | 1X
Aloe Socotrina | 1X 4X 6X 8X 10X 15X
Arsenicum Iodatum | 6X 8X 12X 15X
Asterias Rubens | 4X 6X 8X
Baptisia Tinctoria | 1X 6X 9X 12X 15X
Calcarea Iodata | 8X 10X 12X 30X
Candida Albicans | 12X 15X 20X 30X 60X 200X
Carbo Vegetabilis | 8X 10X 12X
Chelidonium Majus | 1X 2X 12X 15X 30X
Cina | 3X
Cinchona Officinalis | 3X
Colchicum Autumnale | 6X 9X 30X
Echinacea Angustifolia | 1X
Echinacea Purpurea | 1X
Indolum | 10X 12X 15X 30X
Lac Vaccinum | 6X 12X 30X 60X 200X
Lacticum Acidum | 12X 15X 20X 30X 200X
Millefolium | 1X
Saccharum Officinale | 12X 30X 60X 200X
Sarcolacticum Acidum | 30X 200X
Scrophularia Nodosa | 1X 5X 7X 9X 12X 30X
Skatolum | 10X 12X 15X 30X
Solidago Virgaurea | 1X
Sulphur | 12X
Uricum Acidum | 8X 10X 12X 15X

INDICATIONS AND USAGE

Uses:

For temporary relief of minor:

intestinal discomfort*

headaches*

muscle aches*

coughing*

skin itching*

flatulence*

constipation*

*Claims based on traditional homeopathic practice, not accepted medical evidence. Not FDA evaluated.

Warnings:

PREGNANCY OR BREAST FEEDING

If pregnant or breastfeeding, ask a health professional before use.

Do not use if clear seal over the cap is broken or missing.

Keep out of reach of children. In case of overdose, get medical help or contact a Poison Control Center right away.

Stop use and ask a doctor if intestinal discomfort, headaches, muscle aches, coughing, skin itching, flatulence, constipation, or other symptoms do not improve within 7 days or are accompanied by fever.

Directions:

Adults & children ages 12 years and over: Take 5-10 drops under the tongue 2-3 times a day, or as directed by your healthcare professional. Consult a physician for use in children under 12 years of age.

Inactive Ingredients

alcohol (20% by volume), distilled water

Distributed by Apex Energetics. Questions?

16592 Hale Ave., Irvine, CA 92606, USA

PACKAGE LABEL

FUTUREPLEX® A04

ANTITOX®

DEEP

ANTITOX™

Homeopathic Formula

Intestinal Discomfort*

Headaches*

Muscle Aches*

1 fl oz (30 mL)

Alcohol 20% by Volume